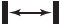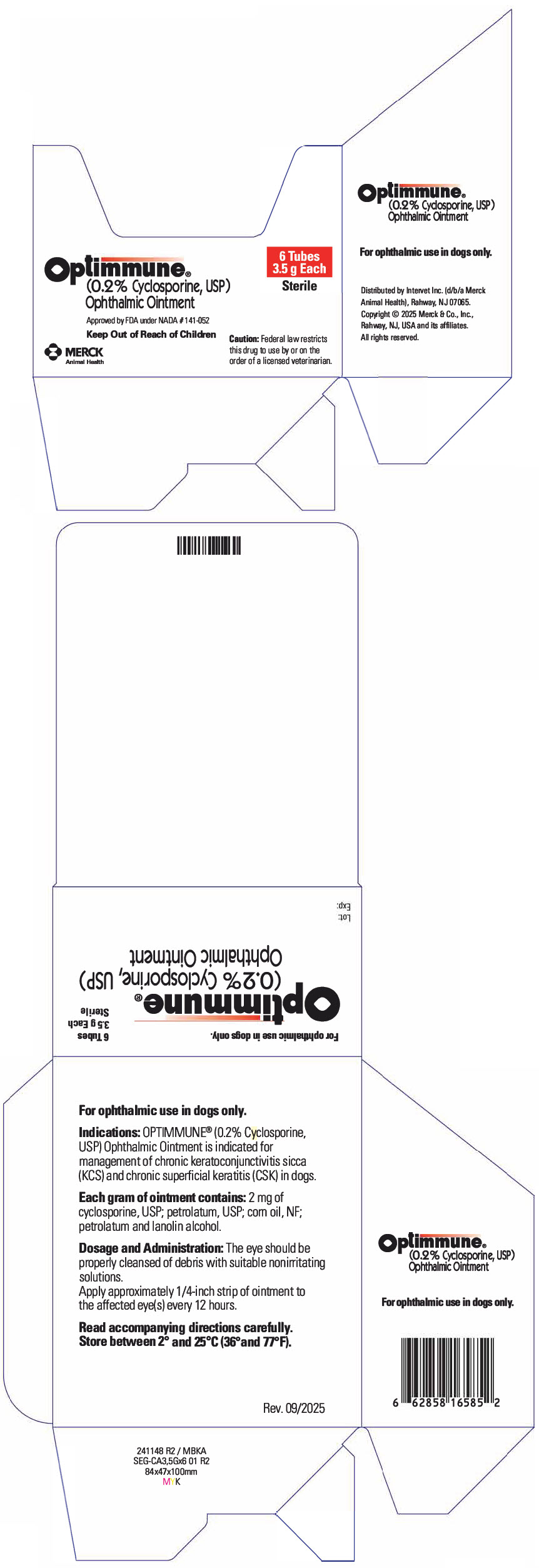 DRUG LABEL: Optimmune Ophthalmic
NDC: 0061-1088 | Form: OINTMENT
Manufacturer: Merck Sharp & Dohme Corp.
Category: animal | Type: PRESCRIPTION ANIMAL DRUG LABEL
Date: 20260116

ACTIVE INGREDIENTS: CYCLOSPORINE 2 mg/1 g

Optimmune® (0.2% Cyclosporine, USP)
Ophthalmic Ointment

Approved by FDA under NADA # 141-052

PRODUCT INFORMATION

For ophthalmic use in dogs only.

Sterile

PRECAUTIONS

CAUTION: US Federal law restricts this drug to use by or on the order of a licensed veterinarian.

DESCRIPTION

DESCRIPTION: Each gram of OPTIMMUNE® Ophthalmic Ointment contains 2 mg of cyclosporine, USP; petrolatum, USP; corn oil, NF; petrolatum and lanolin alcohol. Cyclosporine (cyclosporin A), the active ingredient of OPTIMMUNE Ophthalmic Ointment, is a cyclic undecapeptide metabolite of the fungus Tolypocladium inflatum gams.

MECHANISM OF ACTION

MODE OF ACTION: When applied ophthalmically, cyclosporine is believed to act as a local immunomodulator of diseases suspected to be immune-mediated such as keratoconjunctivitis sicca (KCS) and chronic superficial keratitis (CSK). In the management of KCS, the mechanism by which cyclosporine causes an increase in lacrimation is poorly understood. Clinical improvement in cases of KCS is not necessarily dependent on an increase in aqueous tear production (as measured by the Schirmer Tear Test [STT]). See EFFICACY.

VETERINARY INDICATIONS

INDICATIONS: OPTIMMUNE Ophthalmic Ointment is indicated for management of chronic keratoconjunctivitis sicca (KCS) and chronic superficial keratitis (CSK) in dogs.

PRECAUTIONS

PRECAUTIONS: The clinical effects of OPTIMMUNE Ophthalmic Ointment have not been determined in dogs with KCS due to the following conditions: congenital alacrima, sulfonamide usage, canine distemper virus, metabolic disease, surgical removal of the third eyelid gland, and facial nerve paralysis with loss of the palpebral reflex. Some of the underlying conditions which may lead to KCS can be either transient (e.g., facial nerve trauma) or correctable with appropriate treatment. Consequently, recovery from clinical signs attributed to KCS may be observed and treatment options may need reconsideration.

When switching to cyclosporine from another therapeutic agent (e.g., frequent application of an artificial tear preparation) for KCS or CSK, it should be kept in mind that clinical efficacy is not necessarily apparent immediately after initiation of OPTIMMUNE Ophthalmic Ointment therapy. Several days to a few weeks may be required before the clinical effects of OPTIMMUNE Ophthalmic Ointment are of sufficient magnitude such that previously initiated therapy can be safely withdrawn. Abrupt cessation of a therapeutic agent immediately upon initiation of OPTIMMUNE Ophthalmic Ointment therapy can result in rapid clinical relapse which may be erroneously interpreted as an adverse reaction to OPTIMMUNE Ophthalmic Ointment.

The safety of OPTIMMUNE Ophthalmic Ointment has not been determined in cases of preexisting viral or fungal ocular infections. It is recommended that in such cases, OPTIMMUNE Ophthalmic Ointment therapy be delayed until the fungal/viral ocular infection has been successfully treated.

The safety of OPTIMMUNE Ophthalmic Ointment in puppies, pregnant bitches, or dogs used for breeding has not been determined.

EFFICACY: 1. KCS: A well-controlled clinical field trial was conducted by veterinary ophthalmologists in 9 states and included 132 dogs afflicted with KCS of which 124 were evaluated for efficacy. Dogs were randomly assigned to twice daily (BID) treatment with either 0.2% (OPTIMMUNE Ophthalmic Ointment) or 0% (placebo vehicle) cyclosporine ophthalmic ointment for 12 weeks. Treatment with OPTIMMUNE Ophthalmic Ointment resulted in an average 8 to 9 mm increase in STT by the end of the study period (vs. 3 to 4 mm for the placebo vehicle). Most of the increase in STT, approximately 6 mm, occurred in the first week of therapy. Some dogs improved clinically (i.e., exhibited a decrease in conjunctival and/or corneal pathology) without an increase in STT values. This is thought to occur through suppression of inflammation by cyclosporine on the ocular surface. In this clinical field trial, OPTIMMUNE Ophthalmic Ointment therapy was also associated with an improvement in clinical signs in comparison to the placebo. Blepharitis, blepharospasm, and "other signs of ocular discomfort" (e.g., pawing at eyes), were markedly reduced. Improvement in conjunctival health as manifested by reduced conjunctival hypertrophy, reduced hyperemia, reduced conjunctival discharge volume, and improved character of discharge was evident.

Improvement in corneal health as manifested by improved corneal surface contour, reduced corneal edema, and corneal neovascularization was also noted. Overall improvement was noted in 81% of eyes treated with OPTIMMUNE Ophthalmic Ointment.

Withdrawal of OPTIMMUNE® Ophthalmic Ointment therapy resulted in rapid clinical regression in all but one test eye indicating the need for long-term continual therapy for almost all cases of chronic KCS.

2. CSK: The efficacy of OPTIMMUNE Ophthalmic Ointment was determined in a historical controlled clinical field trial conducted by veterinary ophthalmologists in four countries and included 36 dogs afflicted with CSK. Dogs, primarily German shepherds, a breed disposed to CSK (German shepherd pannus), were treated twice daily with OPTIMMUNE Ophthalmic Ointment for 6 weeks. Clinical improvement was noted by the investigators in 90.3% of eyes treated with OPTIMMUNE Ophthalmic Ointment when compared to baseline.

SAFE HANDLING WARNING

SAFETY: A target animal safety study and clinical field studies with OPTIMMUNE Ophthalmic Ointment showed a wide safety margin in adult dogs. In the 6-month target animal safety study, dogs were subjected twice daily to up to 10 times the approved concentration of OPTIMMUNE Ophthalmic Ointment. No apparent toxicity or adverse reactions were observed. Dogs in this study were vaccinated with commercially available vaccines. No effect on antibody titer response was noted. Epiphora was noted in all groups, including the placebo group, and was not associated with any inflammatory change, nor was there any correlation to gross and histopathological changes.

ADVERSE REACTIONS

ADVERSE REACTIONS: In the KCS clinical field trial, there were 20 adverse reactions reported out of 132 cases enrolled. This corresponds to an adverse reaction rate of 12.9% (13 of 101 cases) for OPTIMMUNE Ophthalmic Ointment treated dogs and 22.6% (7 of 31) for placebo treated dogs. The reactions described were primarily ocular and periocular inflammatory reactions. These were likely a function of therapy being unable to fully control the keratoconjunctivitis, rather than a true "adverse reaction." Similarly, in the CSK trial, of 36 cases evaluated for safety, adverse reactions were noted in 2 animals (5.6%). One involved transient hyperemia, epiphora, and mild discomfort of the eye. The other involved periocular/palpebral inflammation and mild alopecia.

On rare occasion, instillation of OPTIMMUNE Ophthalmic Ointment may be associated with local irritation as manifested by periocular redness, lid spasm, and excessive rubbing. As the eyes of dogs with KCS often demonstrate considerable inflammation, it will be difficult to determine whether this local irritation constitutes a hypersensitivity to OPTIMMUNE Ophthalmic Ointment. If this ocular irritation persists beyond 7 days, hypersensitivity to a component of OPTIMMUNE Ophthalmic Ointment should be suspected and therapeutic options reassessed.

DOSAGE AND ADMINISTRATION: Remove debris with suitable nonirritating solutions. Apply a 1/4-inch strip of ointment to the affected eye(s) every 12 hours. The ointment may be placed directly on the cornea or into the conjunctival sac.

It is recommended that dogs exhibiting chronic recurring conjunctivitis be tested for adequate tear production to determine if they are suffering from early stages of chronic KCS.

For best results in treating KCS, cyclosporine ophthalmic ointment should be administered early in the course of the disease before irreversible damage to the lacrimal tissue, dense corneal scarring, or pigmentation occurs.

Dogs afflicted with KCS or CSK will most likely require lifelong consistent therapy (see EFFICACY section above). For CSK, because environmental factors such as ultraviolet (UV) radiation are implicated in the pathogenesis, clinical signs may subside in the winter months when light intensity is reduced or if the dog is moved to a lower altitude, or indoors, and thus exposed to less UV radiation.^1

In cases refractory to cyclosporine, the diagnosis should be reevaluated and a different course of therapy considered.

Periodic reassessment of the need for OPTIMMUNE Ophthalmic Ointment therapy is recommended.

HOW SUPPLIED

HOW SUPPLIED: OPTIMMUNE Ophthalmic Ointment is available in a 3.5 g tube, carton of 6.

STORAGE AND HANDLING

STORAGE CONDITIONS: Store between 2° and 25° C (36° and 77° F).

KEEP THIS AND ALL DRUGS OUT OF THE REACH OF CHILDREN.

REFERENCES

REFERENCE: ^1Roberts, Steven M. Pannus. In: Kirk's Current Veterinary Therapy XII, Small Animal Practice. Philadelphia: W.B. Saunders Co; 1995:1245-1248.

Formulated in France

Distributed by Intervet Inc. (d/b/a Merck Animal Health), Rahway, NJ 07065.
Copyright © 2025 Merck & Co., Inc., Rahway, NJ, USA and its affiliates.
All rights reserved.

Rev. 09/2025
241145 R3

PRINCIPAL DISPLAY PANEL - 3.5 g Tube Carton

Optimmune®
(0.2% Cyclosporine, USP)
Ophthalmic Ointment

Approved by FDA under NADA # 141-052

Keep Out of Reach of Children

MERCK
Animal Health

6 Tubes
3.5 g Each
Sterile

Caution: Federal law restricts
this drug to use by or on the
order of a licensed veterinarian.